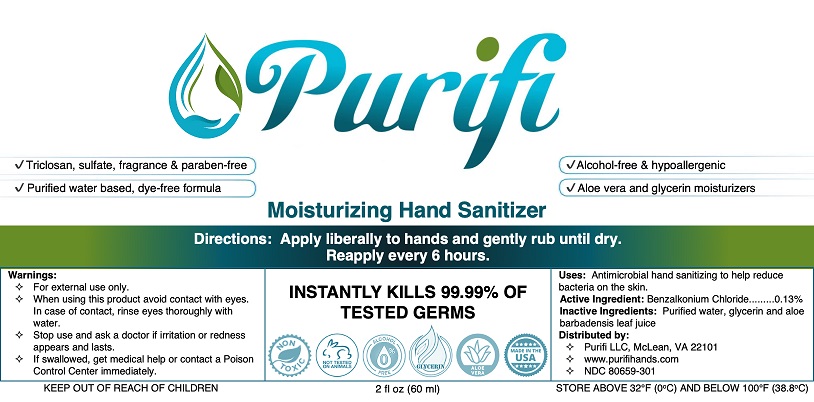 DRUG LABEL: Purifi Hand Sanitizer
NDC: 80659-301 | Form: SOLUTION
Manufacturer: Purifi LLC
Category: otc | Type: HUMAN OTC DRUG LABEL
Date: 20240131

ACTIVE INGREDIENTS: BENZALKONIUM CHLORIDE 0.13 g/100 mL
INACTIVE INGREDIENTS: WATER; ALOE VERA LEAF; GLYCERIN

Purifi Moisturizing Hand Sanitizer
INSTANTLY KILLS 99.99% OF TESTED GERMS

Drug Facts

Active ingredient

Benzalkonium Chloride 0.13%

Purpose

Antimicrobial

Uses

Hand sanitizing to help reduce bacteria on the skin

Warnings

For external use only.

WHEN USING

When using this productavoid contact with the eyes. In case of contact, rinse eyes thoroughly with water.

Stop use and ask a doctor ifirritation or redness appears and lasts

Keep out of reach of children.If swallowed, get medical help or contact a Poison Control Center immediately.

Directions

Apply liberally to hands and gently rub until dry. Reapply every 6 hours.

Other information

Store above 32°F (0°C) and below 100°F (38.8°C)

Inactive ingredients

purified water, glycerin, aloe barbadensis leaf juice